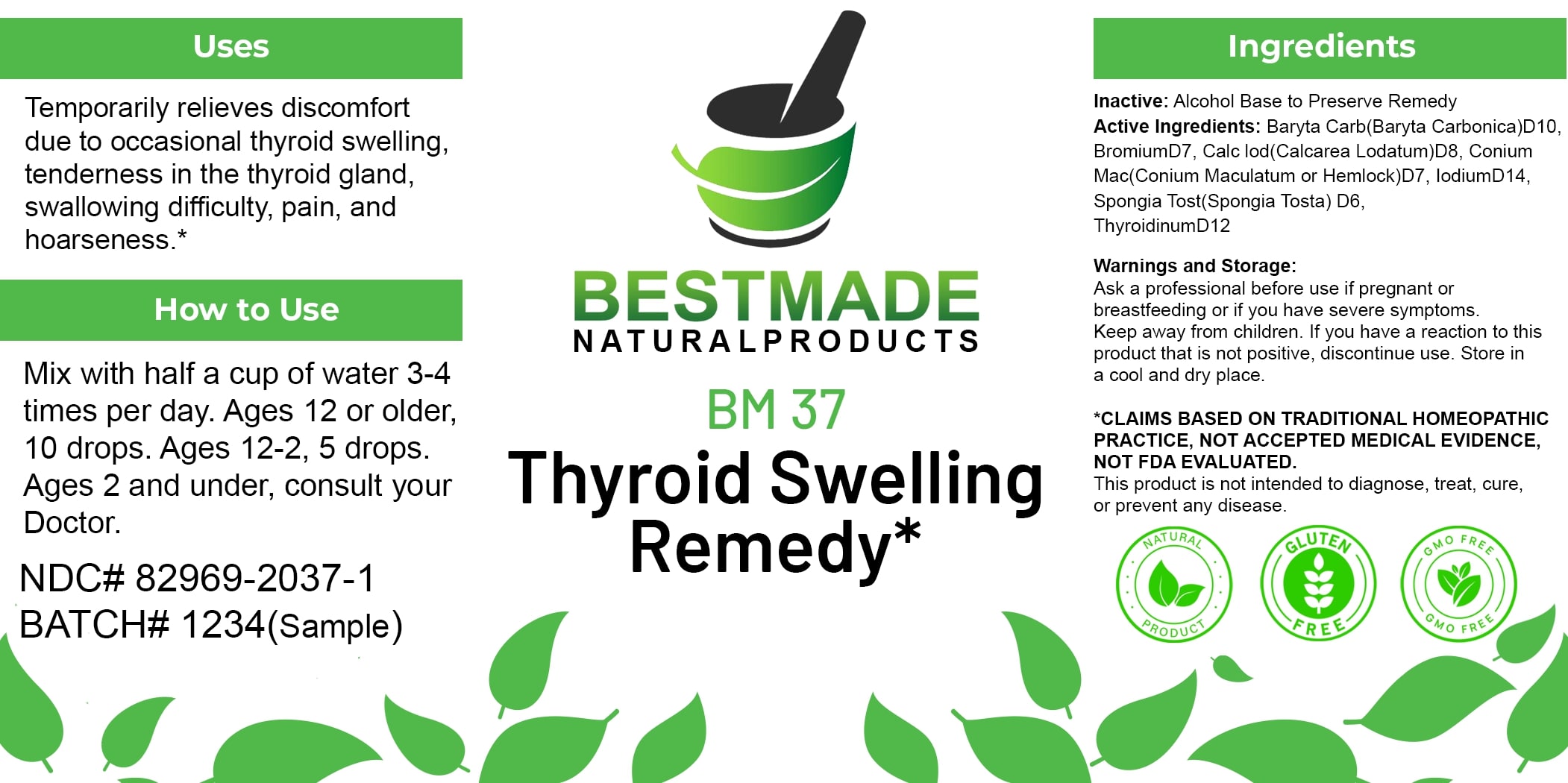 DRUG LABEL: Bestmade Natural Products BM37
NDC: 82969-2037 | Form: LIQUID
Manufacturer: Bestmade Natural Products
Category: homeopathic | Type: HUMAN OTC DRUG LABEL
Date: 20250123

ACTIVE INGREDIENTS: THYROID, UNSPECIFIED 30 [hp_C]/30 [hp_C]; BROMINE 30 [hp_C]/30 [hp_C]; IODINE 30 [hp_C]/30 [hp_C]; SPONGIA OFFICINALIS SKELETON, ROASTED 30 [hp_C]/30 [hp_C]; BARIUM CARBONATE 30 [hp_C]/30 [hp_C]; CONIUM MACULATUM FLOWERING TOP 30 [hp_C]/30 [hp_C]; CALCIUM IODIDE 30 [hp_C]/30 [hp_C]
INACTIVE INGREDIENTS: ALCOHOL 30 [hp_C]/30 [hp_C]

BM37

DOSAGE AND ADMINISTRATION

How to Use

Mix with half a cup of water 3-4 times per day. Ages 12 or older, 10 drops. Ages 12-2, 5 drops. Ages 2 and under, consult your Doctor.

Uses

Temporarily relieves discomfort due to occasional thyroid swelling, tenderness in the thyroid gland, swallowing difficulty, pain, and hoarseness.*

*CLAIMS BASED ON TRADITIONAL HOMEOPATHIC PRACTICE, NOT ACCEPTED MEDICAL EVIDENCE, NOT FDA EVALUATED.

This product is not intended to diagnose, treat, cure, or prevent any disease.

Uses

Temporarily relieves discomfort due to occasional thyroid swelling, tenderness in the thyroid gland, swallowing difficulty, pain, and hoarseness.*

*CLAIMS BASED ON TRADITIONAL HOMEOPATHIC PRACTICE, NOT ACCEPTED MEDICAL EVIDENCE, NOT FDA EVALUATED.

This product is not intended to diagnose, treat, cure, or prevent any disease.

ACTIVE INGREDIENT

Active Ingredients: Baryta Carb (Baryta Carbonica) D10, Bromium D7, Calc Iod (Calcarea Iodatum) D8, Conium Mac (Conium Maculatum or Hemlock) D7, Iodum D14, Spongia Tost (Spongia Tosta) D6, Thyroidinum D12

INACTIVE INGREDIENT

Ingredients

Inactive: Alcohol Base to Preserve Remedy

Warnings and Storage:

Ask a professional before use if pregnant or breastfeeding or if you have severe symptoms. Keep away from children. If you have a reaction to this product that is not positive, discontinue use. Store in a cool and dry place.

*CLAIMS BASED ON TRADITIONAL HOMEOPATHIC PRACTICE, NOT ACCEPTED MEDICAL EVIDENCE, NOT FDA EVALUATED.

This product is not intended to diagnose, treat, cure, or prevent any disease.

KEEP OUT OF REACH OF CHILDREN

Warnings and Storage:

Ask a professional before use if pregnant or breastfeeding or if you have severe symptoms. Keep away from children. If you have a reaction to this product that is not positive, discontinue use. Store in a cool and dry place.

Entire package label